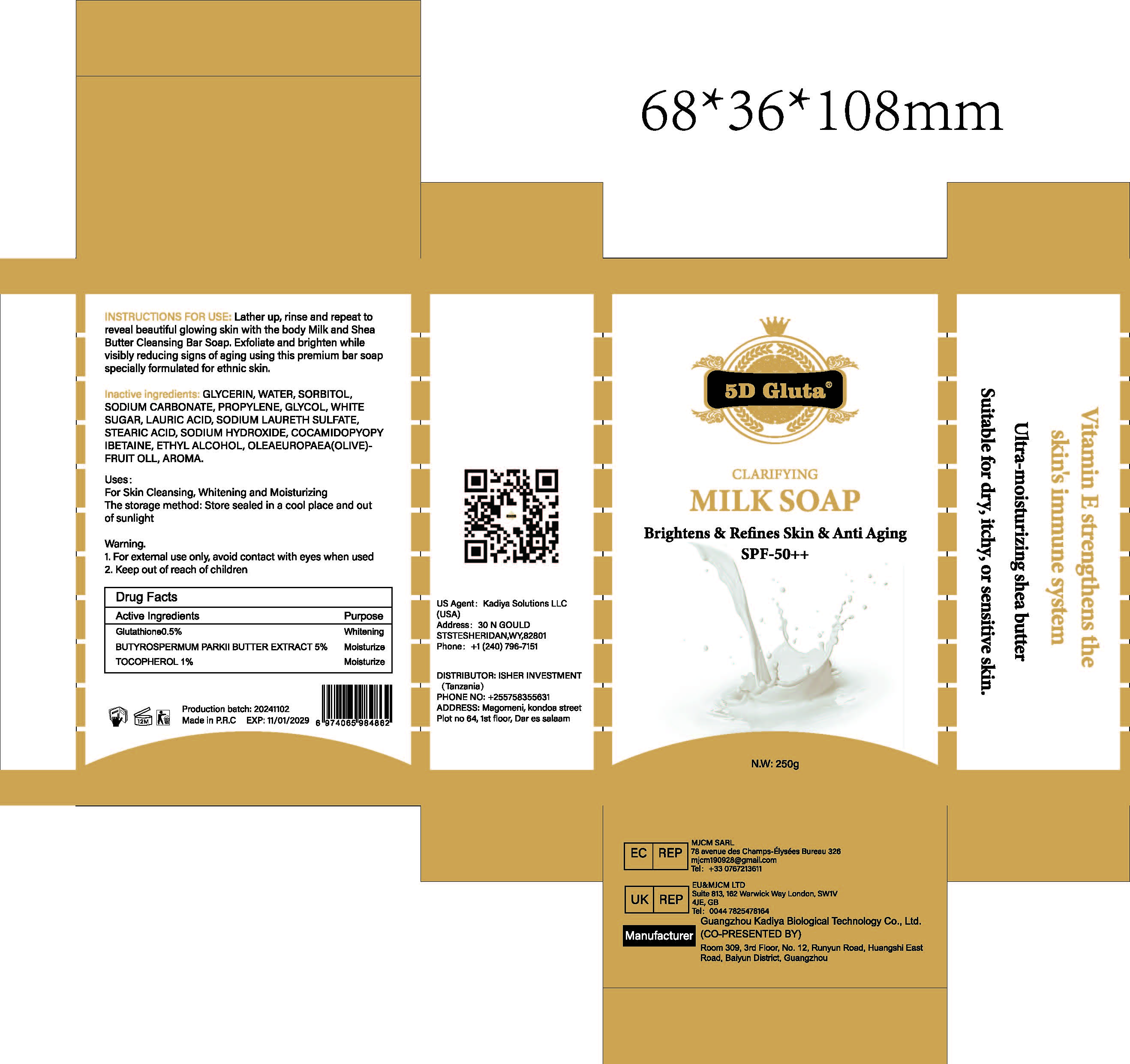 DRUG LABEL: ClarifyingMilkSoap
NDC: 84423-058 | Form: SOAP
Manufacturer: Guangzhou Kadiya Biotechnology Co., Ltd.
Category: otc | Type: HUMAN OTC DRUG LABEL
Date: 20241217

ACTIVE INGREDIENTS: GLUTATHIONE 1.25 g/250 g; TOCOPHEROL 2.5 g/250 g; BUTYROSPERMUM PARKII (SHEA) BUTTER 12.5 g/250 g
INACTIVE INGREDIENTS: SODIUM HYDROXIDE; STEARIC ACID; SODIUM LAURETH SULFATE; WATER; GLYCERIN; SORBITOL; PROPYLENE GLYCOL; SODIUM CARBONATE; LAURIC ACID; COCAMIDOPROPYL BETAINE; ALCOHOL; OLEA EUROPAEA (OLIVE) FRUIT OIL; SUCROSE

PURPOSE

For Skin Cleansing, Whitening and Moisturizing

INACTIVE INGREDIENT

GLYCERIN，WATER，SORBITOL，SODIUM CARBONATE，PROPYLENE，GLYCOL，WHITE SUGAR，LAURIC ACID，SODIUM LAURETH SULFATE，STEARIC ACID ，SODIUM HYDROXIDE，COCAMIDOPYOPY IBETAINE，ETHYL ALCOHOL，OLEAEUROPAEA(OLIVE)FRUIT OLL，AROMA

WARNINGS

1、For external use only, avoid contact with eyes when used
2、Keep out of reach of children

INDICATIONS AND USAGE

Exfoliate and brighten while visibly reducing signs of aging using this premium bar soap specially formulated for ethnic skin.

DOSAGE AND ADMINISTRATION

Lather up, rinse and repeat to reveal beautiful glowing skin with the body Milk and Shea Butter Cleansing Bar Soap.

KEEP OUT OF REACH OF CHILDREN SECTION

Active Ingredients Purpose
Glutathione0.5% Whitening
BUTYROSPERMUM PARKII 5% Moisturize
BUTTER EXTRACT
TOCOPHEROL 1% Moisturize

PACKAGE LABEL

Active Ingredients Purpose
Glutathione0.5% Whitening
BUTYROSPERMUM PARKII 5% Moisturize
BUTTER EXTRACT
TOCOPHEROL 1% Moisturize

Uses：
For Skin Cleansing, Whitening and Moisturizing
The storage method：
Store sealed in a cool place and out of sunlight

Warning.
1、For external use only, avoid contact with eyes when used
2、Keep out of reach of children

Inactive ingredients：
GLYCERIN，WATER，SORBITOL，SODIUM CARBONATE，PROPYLENE，GLYCOL，WHITE SUGAR，LAURIC ACID，SODIUM LAURETH SULFATE，STEARIC ACID ，SODIUM HYDROXIDE，COCAMIDOPYOPY IBETAINE，ETHYL ALCOHOL，OLEAEUROPAEA(OLIVE)FRUIT OLL，AROMA